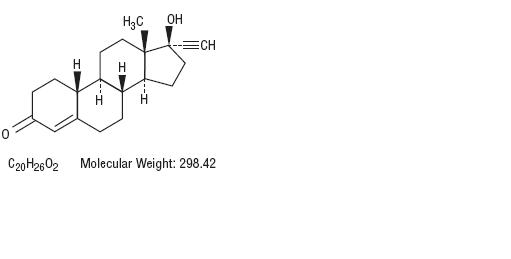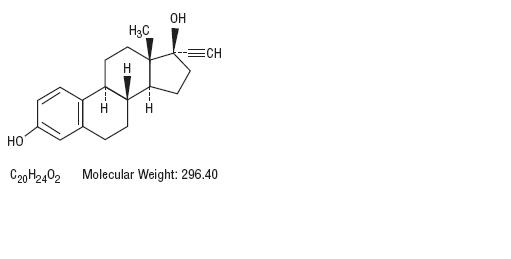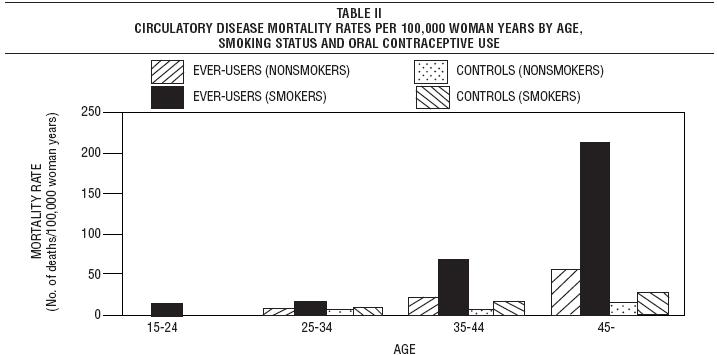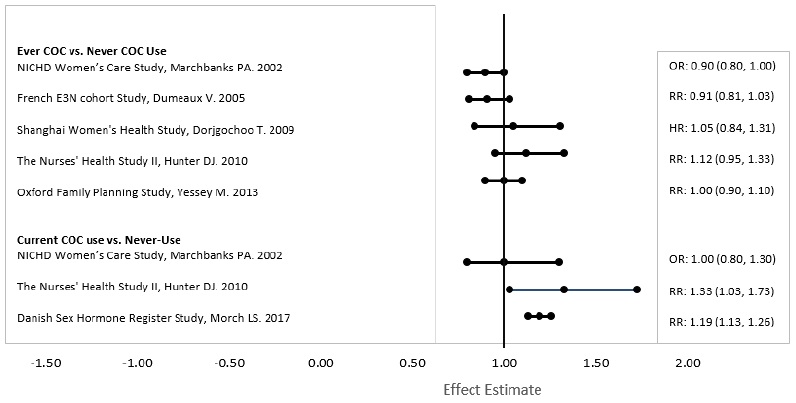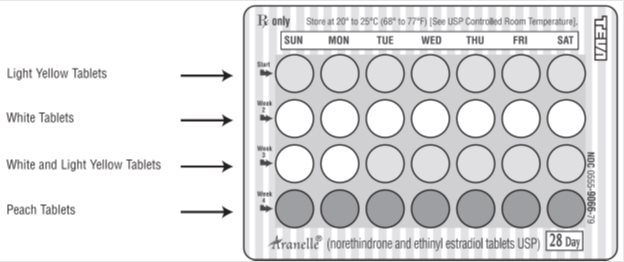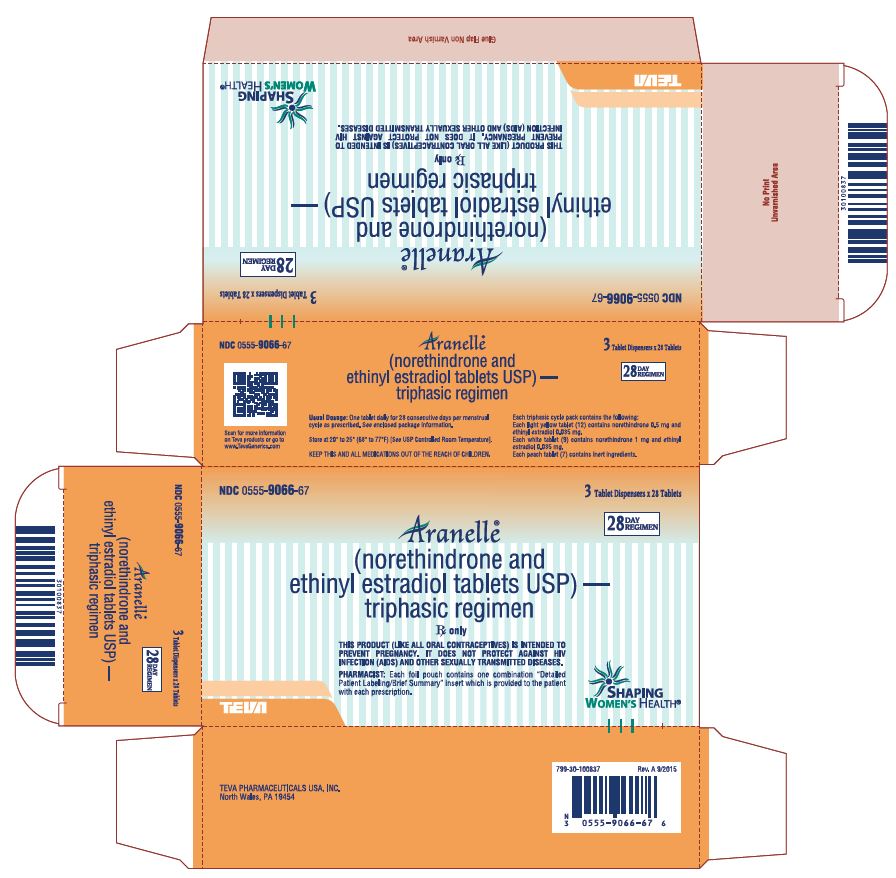 DRUG LABEL: Aranelle
NDC: 0555-9066 | Form: KIT | Route: ORAL
Manufacturer: Teva Pharmaceuticals USA, Inc.
Category: prescription | Type: HUMAN PRESCRIPTION DRUG LABEL
Date: 20230131

ACTIVE INGREDIENTS: NORETHINDRONE 0.5 mg/1 1; ETHINYL ESTRADIOL 0.035 mg/1 1; NORETHINDRONE 1 mg/1 1; ETHINYL ESTRADIOL 0.035 mg/1 1
INACTIVE INGREDIENTS: D&C YELLOW NO. 10 ALUMINUM LAKE; LACTOSE MONOHYDRATE; MAGNESIUM STEARATE; STARCH, CORN; LACTOSE MONOHYDRATE; MAGNESIUM STEARATE; STARCH, CORN; ANHYDROUS LACTOSE; FD&C YELLOW NO. 6; MAGNESIUM STEARATE; MICROCRYSTALLINE CELLULOSE; STARCH, CORN

Aranelle® (norethindrone and ethinyl estradiol tablets, USP)

Patients should be counseled that this product does not protect against HIV infection (AIDS) and other sexually transmitted diseases.

DESCRIPTION

Aranelle® 28-Day Regimen (norethindrone and ethinyl estradiol tablets USP) provides a continuous oral contraceptive regimen of 7 light yellow tablets, 9 white tablets, 5 more light yellow tablets, and then 7 peach tablets. Each light yellow tablet contains norethindrone, USP 0.5 mg and ethinyl estradiol, USP 0.035 mg, each white tablet contains norethindrone, USP 1 mg and ethinyl estradiol, USP 0.035 mg, and each peach tablet contains inert ingredients.

Norethindrone, USP is a potent progestational agent with the chemical name 17-Hydroxy-19-nor-17α-pregn-4-en-20-yn-3-one. Ethinyl estradiol, USP is an estrogen with the chemical name 19-Nor-17α-pregna-1,3,5(10)-trien-20-yne-3,17-diol. Their structural formulae follow.

Norethindrone, USP

Ethinyl Estradiol, USP

The light yellow tablet contains the following inactive ingredients, D&C yellow no. 10 aluminum lake, lactose monohydrate, magnesium stearate, and pregelatinized starch.

The white tablet contains the following inactive ingredients, lactose monohydrate, magnesium stearate, and pregelatinized starch.

The inactive peach tablets contain the following inactive ingredients, anhydrous lactose, FD&C yellow no. 6 aluminum lake, magnesium stearate, microcrystalline cellulose, and pregelatinized starch.

CLINICAL PHARMACOLOGY

Combination oral contraceptives act by suppression of gonadotrophins. Although the primary mechanism of this action is inhibition of ovulation, other alterations include changes in the cervical mucus (which increase the difficulty of sperm entry into the uterus) and the endometrium (which may reduce the likelihood of implantation).

INDICATIONS AND USAGE

Oral contraceptives are indicated for the prevention of pregnancy in women who elect to use this product as a method of contraception.

Oral contraceptive products which contain 50 mcg of estrogen, should not be used unless medically indicated.

Oral contraceptives are highly effective. Table I lists the typical accidental pregnancy rates for users of combination oral contraceptives and other methods of contraception.^1 The efficacy of these contraceptive methods, except sterilization, depends upon the reliability with which they are used. Correct and consistent use of methods can result in lower failure rates.

TABLE I: PERCENTAGE OF WOMEN EXPERIENCING AN UNINTENDED PREGNANCY DURING THE FIRST YEAR OF TYPICAL USE AND THE FIRST YEAR OF PERFECT USE OF CONTRACEPTION AND THE PERCENTAGE CONTINUING USE AT THE END OF THE FIRST YEAR. UNITED STATES.
 | % of Women Experiencing an Unintended Pregnancy within the First Year of Use |  | % of Women Continuing Use at One Year^3
Method; (1) | Typical Use^1; (2) | Perfect Use^2; (3) | (4)
Chance^4 | 85 | 85
Spermicides^5 | 26 | 6 | 40
Periodic abstinence | 25 |  | 63
Calendar |  | 9
Ovulation method |  | 3
Sympto-thermal^6 |  | 2
Post-ovulation |  | 1
Withdrawal | 19 | 4
Cap^7
Parous women | 40 | 26 | 42
Nulliparous women | 20 | 9 | 56
Sponge
Parous women | 40 | 20 | 42
Nulliparous women | 20 | 9 | 56
Diaphragm^7 | 20 | 6 | 56
Condom^8
Female (Reality) | 21 | 5 | 56
Male | 14 | 3 | 61
Pill | 5 |  | 71
Progestin only |  | 0.5
Combined |  | 0.1
IUD
Progesterone T | 2 | 1.5 | 81
Copper T 380A | 0.8 | 0.6 | 78
LNg 20 | 0.1 | 0.1 | 81
Depo-Provera | 0.3 | 0.3 | 70
Norplant and Norplant-2 | 0.05 | 0.05 | 88
Female sterilization | 0.5 | 0.5 | 100
Male sterilization | 0.15 | 0.10 | 100
Emergency Contraceptive Pills: Treatment initiated within 72 hours after unprotected intercourse reduces the risk of pregnancy by at least 75%.^9
Lactational Amenorrhea Method: LAM is a highly effective, temporary method of contraception.^10
Source: Trussell J. Contraceptive Efficacy Table from Hatcher R.A., Trussell J, Stewart F, Cates W, Stewart GK, Kowal D, Guest F, in Contraceptive Technology: Seventeenth Revised Edition. New York, NY: Irvington Publishers, 1998.
1. Among typical couples who initiate use of a method (not necessarily for the first time), the percentage who experience an accidental pregnancy during the first year if they do not stop use for any other reason.
2. Among couples who initiate use of a method (not necessarily for the first time) and who use it perfectly (both consistently and correctly), the percentage who experience an accidental pregnancy during the first year if they do not stop use for any other reason.
3. Among couples attempting to avoid pregnancy, the percentage who continue to use a method for one year.
4. The percents becoming pregnant in columns (2) and (3) are based on data from populations where contraception is not used and from women who cease using contraception in order to become pregnant. Among such populations, about 89% become pregnant within one year. This estimate was lowered slightly (to 85%) to represent the percent who would become pregnant within one year among women now relying on reversible methods of contraception if they abandoned contraception altogether.
5. Foams, creams, gels, vaginal suppositories, and vaginal film.
6. Cervical mucus (ovulation) method supplemented by calendar in the pre-ovulatory and basal body temperature in the post-ovulatory phases.
7. With spermicidal cream or jelly.
8. Without spermicides.
9. The treatment schedule is one dose within 72 hours after unprotected intercourse and a second dose 12 hours after the first dose. The Food and Drug Administration has declared the following brands of oral contraceptives to be safe and effective for emergency contraception: Ovral (1 dose is 2 white pills), Alesse (1 dose is 5 pink pills), Nordette or Levlen (1 dose is 2 light-orange pills), Lo/Ovral (1 dose is 4 white pills), Triphasil or Tri-Levlen (1 dose is 4 yellow pills).
10. However, to maintain effective protection against pregnancy, another method of contraception must be used as soon as menstruation resumes, the frequency or duration of breastfeeds is reduced, bottle feeds are introduced, or the baby reaches six months of age.

CONTRAINDICATIONS

Oral contraceptives should not be used in women who have the following conditions:

- Thrombophlebitis or thromboembolic disorders
- A past history of deep vein thrombophlebitis or thromboembolic disorders
- Cerebral vascular or coronary artery disease
- Current diagnosis of, or history of, breast cancer, which may be hormone-sensitive
- Undiagnosed abnormal genital bleeding
- Cholestatic jaundice of pregnancy or jaundice with prior pill use
- Hepatic adenomas, carcinomas or benign liver tumors
- Known or suspected pregnancy
- Are receiving Hepatitis C drug combinations containing ombitasvir/paritaprevir/ritonavir, with or without dasabuvir, due to potential for ALT elevations (see WARNINGS, Risk of Liver Enzyme Elevations with Concomitant Hepatitis C Treatment).

WARNINGS

BOXED WARNING

Cigarette smoking increases the risk of serious cardiovascular side effects from oral contraceptive use. This risk increases with age and with heavy smoking (15 or more cigarettes per day) and is quite marked in women over 35 years of age. Women who use oral contraceptives should be strongly advised not to smoke.

The use of oral contraceptives is associated with increased risks of several serious conditions including myocardial infarction, thromboembolism, stroke, hepatic neoplasia, and gallbladder disease, although the risk of serious morbidity or mortality is very small in healthy women without underlying risk factors. The risk of morbidity and mortality increases significantly in the presence of other underlying risk factors such as hypertension, hyperlipidemias, hypercholesterolemia, obesity and diabetes.^2-5

Practitioners prescribing oral contraceptives should be familiar with the following information relating to these risks.

The information contained in this package insert is principally based on studies carried out in patients who used oral contraceptives with higher formulations of both estrogens and progestogens than those in common use today.^6-11 The effect of long-term use of the oral contraceptives with lower formulations of both estrogens and progestogens remains to be determined.

Throughout this labeling, epidemiological studies reported are of two types: retrospective or case control studies and prospective or cohort studies. Case control studies provide a measure of the relative risk of a disease. Relative risk, the ratio of the incidence of a disease among oral contraceptive users to that among non-users, cannot be assessed directly from case control studies, but the odds ratio obtained is a measure of relative risk. The relative risk does not provide information on the actual clinical occurrence of a disease. Cohort studies provide not only a measure of the relative risk but a measure of attributable risk, which is the difference in the incidence of disease between oral contraceptive users and non-users. The attributable risk does provide information about the actual occurrence of a disease in the population (adapted from ref. 12 and 13 with the author’s permission). For further information, the reader is referred to a text on epidemiological methods.

1. Thromboembolic Disorders and Other Vascular Problems

a. Myocardial Infarction

An increased risk of myocardial infarction has been attributed to oral contraceptive use. This risk is primarily in smokers or women with other underlying risk factors for coronary artery disease such as hypertension, hypercholesterolemia, morbid obesity and diabetes.^(2-5, 13) The relative risk of heart attack for current oral contraceptive users has been estimated to be 2 to 6.^(2, 14-19) The risk is very low under the age of 30. However, there is the possibility of a risk of cardiovascular disease even in very young women who take oral contraceptives.

Smoking in combination with oral contraceptive use has been shown to contribute substantially to the incidence of myocardial infarctions in women in their mid-thirties or older, with smoking accounting for the majority of excess cases.^20

Mortality rates associated with circulatory disease have been shown to increase substantially in smokers over the age of 35 and non-smokers over the age of 40 among women who use oral contraceptives (see Table II).^16

Adapted from P.M. Layde and V. Beral, Table V^16

Oral contraceptives may compound the effects of well-known risk factors such as hypertension, diabetes, hyperlipidemias, hypercholesterolemia, age and obesity.^(3, 13, 21) In particular, some progestogens are known to decrease HDL cholesterol and cause glucose intolerance, while estrogens may create a state of hyperinsulinism.^21-25 Oral contraceptives have been shown to increase blood pressure among users (see WARNINGS, Elevated Blood Pressure). Similar effects on risk factors have been associated with an increased risk of heart disease. Oral contraceptives must be used with caution in women with cardiovascular disease risk factors.

b. Thromboembolism

An increased risk of thromboembolic and thrombotic disease associated with the use of oral contraceptives is well established. Case control studies have found the relative risk of users compared to non-users to be 3 for the first episode of superficial venous thrombosis, 4 to 11 for deep vein thrombosis or pulmonary embolism, and 1.5 to 6 for women with predisposing conditions for venous thromboembolic disease.^(12, 13, 26-31) Cohort studies have shown the relative risk to be somewhat lower, about 3 for new cases and about 4.5 for new cases requiring hospitalization.^32 The risk of thromboembolic disease due to oral contraceptives is not related to length of use and disappears after pill use is stopped.^12

A 2- to 6-fold increase in relative risk of post-operative thromboembolic complications has been reported with the use of oral contraceptives. The relative risk of venous thrombosis in women who have predisposing conditions is twice that of women without such medical conditions.^83 If feasible, oral contraceptives should be discontinued at least 4 weeks prior to and for 2 weeks after elective surgery and during and following prolonged immobilization. Since the immediate postpartum period also is associated with an increased risk of thromboembolism, oral contraceptives should be started no earlier than 4 to 6 weeks after delivery in women who elect not to breast feed.^33

c. Cerebrovascular Diseases

An increase in both the relative and attributable risks of cerebrovascular events (thrombotic and hemorrhagic strokes) has been shown in users of oral contraceptives. In general, the risk is greatest among older (>35 years), hypertensive women who also smoke. Hypertension was found to be a risk factor for both users and non-users for both types of strokes while smoking interacted to increase the risk for hemorrhagic strokes.^34

In a large study, the relative risk of thrombotic strokes has been shown to range from 3 for normotensive users to 14 for users with severe hypertension.^35 The relative risk of hemorrhagic stroke is reported to be 1.2 for non-smokers who used oral contraceptives, 2.6 for smokers who did not use oral contraceptives, 7.6 for smokers who used oral contraceptives, 1.8 for normotensive users and 25.7 for users with severe hypertension.^35 The attributable risk also is greater in women in their mid-thirties or older and among smokers.^13

d. Dose-Related Risk of Vascular Disease from Oral Contraceptives

A positive association has been observed between the amount of estrogen and progestogen in oral contraceptives and the risk of vascular disease.^36-38 A decline in serum high density lipoproteins (HDL) has been reported with many progestational agents.^22-24 A decline in serum high density lipoproteins has been associated with an increased incidence of ischemic heart disease.^39 Because estrogens increase HDL cholesterol, the net effect of an oral contraceptive depends on a balance achieved between doses of estrogen and progestogen and the nature and absolute amount of progestogens used in the contraceptives. The amount of both hormones should be considered in the choice of an oral contraceptive.^37

Minimizing exposure to estrogen and progestogen is in keeping with good principles of therapeutics. For any particular estrogen/progestogen combination, the dosage regimen prescribed should be one which contains the least amount of estrogen and progestogen that is compatible with a low failure rate and the needs of the individual patient. New acceptors of oral contraceptive agents should be started on preparations containing the lowest estrogen content that produces satisfactory results for the individual. Products containing 50 mcg estrogen should be used only when medically indicated.

e. Persistence of Risk of Vascular Disease

There are three studies which have shown persistence of risk of vascular disease for ever-users of oral contraceptives.^(17, 34, 40) In a study in the United States, the risk of developing myocardial infarction after discontinuing oral contraceptives persists for at least 9 years for women 40 to 49 years who had used oral contraceptives for 5 or more years, but this increased risk was not demonstrated in other age groups.^17 In another study in Great Britain, the risk of developing cerebrovascular disease persisted for at least 6 years after discontinuation of oral contraceptives, although excess risk was very small.^40 There is a significantly increased relative risk of subarachnoid hemorrhage after termination of use of oral contraceptives.^34 However, these studies were performed with oral contraceptive formulations containing 50 mcg or higher of estrogen. Products containing 50 mcg estrogen should be used only when medically indicated.

2. Estimates of Mortality from Contraceptive Use

One study gathered data from a variety of sources which have estimated the mortality rates associated with different methods of contraception at different ages (see Table III).^41 These estimates include the combined risk of death associated with contraceptive methods plus the risk attributable to pregnancy in the event of method failure. Each method of contraception has its specific benefits and risks. The study concluded that with the exception of oral contraceptive users 35 and older who smoke and 40 and older who do not smoke, mortality associated with all methods of birth control is low and below that associated with childbirth. The observation of a possible increase in risk of mortality with age for oral contraceptive users is based on data gathered in the 1970s -- but not reported in the U.S. until 1983.^(16, 41) However, current clinical practice involves the use of lower estrogen dose formulations combined with careful restriction of oral contraceptive use to women who do not have the various risk factors listed in this labeling.

Because of these changes in practice and, also, because of some limited new data which suggest that the risk of cardiovascular disease with the use of oral contraceptives may now be less than previously observed,^(78, 79) the Fertility and Maternal Health Drugs Advisory Committee was asked to review the topic in 1989. The Committee concluded that although cardiovascular disease risks may be increased with oral contraceptive use after age 40 in healthy non-smoking women (even with the newer low-dose formulations), there are greater potential health risks associated with pregnancy in older women and with the alternative surgical and medical procedures which may be necessary if such women do not have access to effective and acceptable means of contraception.

Therefore, the Committee recommended that the benefits of oral contraceptive use by healthy non-smoking women over 40 may outweigh the possible risks. Of course, older women, as all women who take oral contraceptives, should take the lowest possible dose formulation that is effective.^80

TABLE III: ESTIMATED ANNUAL NUMBER OF BIRTH-RELATED OR METHOD-RELATED DEATHS ASSOCIATED WITH CONTROL OF FERTILITY PER 100,000 NONSTERILE WOMEN, BY FERTILITY CONTROL METHOD ACCORDING TO AGE
 |  |  | Age
Method of Control and Outcome | 15 to 19 | 20 to 24 | 25 to 29 | 30 to 34 | 35 to 39 | 40 to 44
No fertility control methods* | 7 | 7.4 | 9.1 | 14.8 | 25.7 | 28.2
Oral contraceptives non-smoker** smoker** | 0.3 2.2 | 0.5 3.4 | 0.9 6.6 | 1.9 13.5 | 13.8 51.1 | 31.6 117.2
IUD** | 0.8 | 0.8 | 1 | 1 | 1.4 | 1.4
Condom* | 1.1 | 1.6 | 0.7 | 0.2 | 0.3 | 0.4
Diaphragm/Spermicide* | 1.9 | 1.2 | 1.2 | 1.3 | 2.2 | 2.8
Periodic abstinence* | 2.5 | 1.6 | 1.6 | 1.7 | 2.9 | 3.6

* Deaths are birth-related

** Deaths are method-related

Estimates adapted from H.W. Ory, Table 3^41

3. Malignant Neoplasms

Breast Cancer

Aranelle is contraindicated in females who currently have or have had breast cancer because breast cancer may be hormonally sensitive (see CONTRAINDICATIONS).

Epidemiology studies have not found a consistent association between use of combined oral contraceptives (COCs) and breast cancer risk. Studies do not show an association between ever (current or past) use of COCs and risk of breast cancer. However, some studies report a small increase in the risk of breast cancer among current or recent users (<6 months since last use) and current users with longer duration of COC use (see Postmarketing Experience).

Cervical Cancer

Some studies suggest that oral contraceptive use has been associated with an increase in the risk of cervical intraepithelial neoplasia in some populations of women.^50-53 However, there continues to be controversy about the extent to which such findings may be due to differences in sexual behavior and other factors.

In spite of many studies of the relationship between oral contraceptive use and breast or cervical cancers, a cause-and-effect relationship has not been established.

4. Hepatic Neoplasia

Benign hepatic adenomas are associated with oral contraceptive use although the incidence of benign tumors is rare in the United States. Indirect calculations have estimated the attributable risk to be in the range of 3.3 cases per 100,000 for users, a risk that increases after 4 or more years of use.^54 Rupture of rare, benign, hepatic adenomas may cause death through intra-abdominal hemorrhage.^55-56

Studies in the United States and Britain have shown an increased risk of developing hepatocellular carcinoma in long-term (>8 years) oral contraceptive users.^57-59 However, these cancers are rare in the U.S. and the attributable risk (the excess incidence) of liver cancers in oral contraceptive users approaches less than 1 per 1,000,000 users.

5. Risk of Liver Enzyme Elevations with Concomitant Hepatitis C Treatment

During clinical trials with the Hepatitis C combination drug regimen that contains ombitasvir/paritaprevir/ritonavir, with or without dasabuvir, ALT elevations greater than 5 times the upper limit of normal (ULN), including some cases greater than 20 times the ULN, were significantly more frequent in women using ethinyl estradiol-containing medications such as COCs. Discontinue Aranelle® prior to starting therapy with the combination drug regimen ombitasvir/paritaprevir/ritonavir, with or without dasabuvir [see Contraindications]. Aranelle® can be restarted approximately 2 weeks following completion of treatment with the combination drug regimen.

6. Ocular Lesions

There have been clinical case reports of retinal thrombosis associated with the use of oral contraceptives. Oral contraceptives should be discontinued if there is unexplained partial or complete loss of vision; onset of proptosis or diplopia; papilledema; or retinal vascular lesions. Appropriate diagnostic and therapeutic measures should be undertaken immediately.

7. Oral Contraceptive Use Before or During Early Pregnancy

Extensive epidemiological studies have revealed no increased risk of birth defects in women who have used oral contraceptives prior to pregnancy.^60-62 Studies also do not suggest a teratogenic effect, particularly insofar as cardiac anomalies and limb reduction defects are concerned, when taken inadvertently during early pregnancy.^60,61,63,64

The administration of oral contraceptives to induce withdrawal bleeding should not be used as a test for pregnancy. Oral contraceptives should not be used during pregnancy to treat threatened or habitual abortion.

It is recommended that for any patient who has missed 2 consecutive periods, pregnancy should be ruled out before continuing oral contraceptive use. If the patient has not adhered to the prescribed schedule, the possibility of pregnancy should be considered at the first missed period. Oral contraceptive use should be discontinued if pregnancy is confirmed.

8. Gallbladder Disease

Earlier studies have reported an increased lifetime relative risk of gallbladder surgery in users of oral contraceptives and estrogens.^65-66 More recent studies, however, have shown that the relative risk of developing gallbladder disease among oral contraceptive users may be minimal.^67 The recent findings of minimal risk may be related to the use of oral contraceptive formulations containing lower hormonal doses of estrogens and progestogens.^68

9. Carbohydrate and Lipid Metabolic Effects

Oral contraceptives have been shown to cause glucose intolerance in a significant percentage of users.^25 Oral contraceptives containing greater than 75 mcg of estrogen cause hyperinsulinism, while lower doses of estrogen cause less glucose intolerance.^70 Progestogens increase insulin secretion and create insulin resistance, this effect varying with different progestational agents.^(25, 71) However, in the non-diabetic woman, oral contraceptives appear to have no effect on fasting blood glucose.^69 Because of these demonstrated effects, prediabetic and diabetic women should be carefully observed while taking oral contraceptives.

Some women may develop persistent hypertriglyceridemia while on the pill.^72 As discussed earlier (see WARNINGS, Myocardial Infarction and Dose-Related Risk of Vascular Disease from Oral Contraceptives), changes in serum triglycerides and lipoprotein levels have been reported in oral contraceptive users.^23

10. Elevated Blood Pressure

An increase in blood pressure has been reported in women taking oral contraceptives and this increase is more likely in older oral contraceptive users and with continued use.^(73, 84) Data from the Royal College of General Practitioners and subsequent randomized trials have shown that the incidence of hypertension increases with increasing concentrations of progestogens.

Women with a history of hypertension or hypertension-related diseases or renal disease should be encouraged to use another method of contraception. If women elect to use oral contraceptives, they should be monitored closely and if significant elevation of blood pressure occurs oral contraceptives should be discontinued. For most women, elevated blood pressure will return to normal after stopping oral contraceptives and there is no difference in the occurrence of hypertension among ever- and never-users.^73-75

11. Headache

The onset or exacerbation of migraine or development of headache with a new pattern which is recurrent, persistent or severe requires discontinuation of oral contraceptives and evaluation of the cause.

12. Bleeding Irregularities

Breakthrough bleeding and spotting are sometimes encountered in patients on oral contraceptives, especially during the first 3 months of use. Non-hormonal causes should be considered and adequate diagnostic measures taken to rule out malignancy or pregnancy in the event of breakthrough bleeding, as in the case of any abnormal vaginal bleeding. If pathology has been excluded, time or a change to another formulation may solve the problem. In the event of amenorrhea, pregnancy should be ruled out.

Some women may encounter post-pill amenorrhea or oligomenorrhea, especially when such a condition was pre-existent.

PRECAUTIONS

General

Patients should be counseled that this product does not protect against HIV infection (AIDS) and other sexually transmitted diseases.

1. Physical Examination and Follow-Up

It is good medical practice for all women to have annual history and physical examinations, including women using oral contraceptives. The physical examination, however, may be deferred until after initiation of oral contraceptives if requested by the woman and judged appropriate by the clinician. The physical examination should include special reference to blood pressure, breasts, abdomen and pelvic organs, including cervical cytology, and relevant laboratory tests. In case of undiagnosed, persistent or recurrent abnormal vaginal bleeding, appropriate measures should be conducted to rule out malignancy. Women with a strong family history of breast cancer or who have breast nodules should be monitored with particular care.

2. Lipid Disorders

Women who are being treated for hyperlipidemias should be followed closely if they elect to use oral contraceptives. Some progestogens may elevate LDL levels and may render the control of hyperlipidemias more difficult.

3. Liver Function

If jaundice develops in any woman receiving oral contraceptives the medication should be discontinued. Steroid hormones may be poorly metabolized in patients with impaired liver function.

4. Fluid Retention

Oral contraceptives may cause some degree of fluid retention. They should be prescribed with caution, and only with careful monitoring, in patients with conditions which might be aggravated by fluid retention.

5. Emotional Disorders

Women with a history of depression should be carefully observed and the drug discontinued if depression recurs to a serious degree.

6. Contact Lenses

Contact lens wearers who develop visual changes or changes in lens tolerance should be assessed by an ophthalmologist.

7. Drug Interactions

Reduced efficacy and increased incidence of breakthrough bleeding and menstrual irregularities have been associated with concomitant use of rifampin. A similar association though less marked, has been suggested with barbiturates, phenylbutazone, phenytoin sodium, and possibly with griseofulvin, ampicillin and tetracyclines.^76

Concomitant Use with HCV Combination Therapy – Liver Enzyme Elevation

Do not coadminister Aranelle® with HCV drug combinations containing ombitasvir/paritaprevir/ritonavir, with or without dasabuvir, due to potential for ALT elevations (see WARNINGS, Risk of Liver Enzyme Elevations with Concomitant Hepatitis C Treatment).

8. Interactions with Laboratory Tests

Certain endocrine and liver function tests and blood components may be affected by oral contraceptives:

a. Increased prothrombin and factors VII, VIII, IX, and X; decreased antithrombin 3; increased
norepinephrine-induced platelet aggregability.

b. Increased thyroid binding globulin (TBG) leading to increased circulating total thyroid hormone, as measured by protein-bound iodine (PBI), T4 by column or by radioimmunoassay. Free T3 resin uptake is decreased, reflecting the elevated TBG. Free T4 concentration is unaltered.

c. Other binding proteins may be elevated in serum.

d. Sex steroid binding globulins are increased and result in elevated levels of total circulating sex steroids and corticoids; however, free or biologically active levels remain unchanged.

e. Triglycerides may be increased.

f. Glucose tolerance may be decreased.

g. Serum folate levels may be depressed by oral contraceptive therapy. This may be of clinical significance if a woman becomes pregnant shortly after discontinuing oral contraceptives.

9. Carcinogenesis

See WARNINGS section.

10. Pregnancy

See CONTRAINDICATIONS and WARNINGS sections.

11. Nursing Mothers

Small amounts of oral contraceptive steroids have been identified in the milk of nursing mothers and a few adverse effects on the child have been reported, including jaundice and breast enlargement. In addition, oral contraceptives given in the postpartum period may interfere with lactation by decreasing the quantity and quality of breast milk. If possible, the nursing mother should be advised not to use oral contraceptives but to use other forms of contraception until she has completely weaned her child.

12. Pediatric Use

Safety and efficacy of Aranelle® have been established in women of reproductive age. Safety and efficacy are expected to be the same for postpubertal adolescents under the age of 16 and for users 16 years and older. Use of the product before menarche is not indicated.

INFORMATION FOR THE PATIENT

See PATIENT LABELING printed below.

ADVERSE REACTIONS

Post Marketing Experience

Five studies that compared breast cancer risk between ever-users (current or past use) of COCs and never-users of COCs reported no association between ever use of COCs and breast cancer risk, with effect estimates ranging from 0.90 to 1.12 (Figure 1).

Three studies compared breast cancer risk between current or recent COC users (<6 months since last use) and never users of COCs (Figure 1). One of these studies reported no association between breast cancer risk and COC use. The other two studies found an increased relative risk of 1.19 to 1.33 with current or recent use. Both of these studies found an increased risk of breast cancer with current use of longer duration, with relative risks ranging from 1.03 with less than one year of COC use to approximately 1.4 with more than 8 to 10 years of COC use.

Figure 1. Relevant Studies of Risk of Breast Cancer with Combined Oral Contraceptives

RR = relative risk; OR = odds ratio; HR = hazard ratio. “ever COC” are females with current or past COC use; “never COC use” are females that never used COCs.

An increased risk of the following serious adverse reactions has been associated with the use of oral contraceptives (see WARNINGS section):

- Thrombophlebitis
- Arterial thromboembolism
- Pulmonary embolism
- Myocardial infarction
- Cerebral hemorrhage
- Cerebral thrombosis
- Hypertension
- Gallbladder disease
- Hepatic adenomas, carcinomas or benign liver tumors

There is evidence of an association between the following conditions and the use of oral contraceptives, although additional confirmatory studies are needed:

- Mesenteric thrombosis
- Retinal thrombosis

The following adverse reactions have been reported in patients receiving oral contraceptives and are believed to be drug-related:

- Nausea
- Vomiting
- Gastrointestinal symptoms (such as abdominal cramps and bloating)
- Breakthrough bleeding
- Spotting
- Change in menstrual flow
- Amenorrhea
- Temporary infertility after discontinuation of treatment
- Edema
- Melasma which may persist
- Breast changes: tenderness, enlargement, secretion
- Change in weight (increase or decrease)
- Change in cervical erosion and secretion
- Diminution in lactation when given immediately postpartum
- Cholestatic jaundice
- Migraine
- Rash (allergic)
- Mental depression
- Reduced tolerance to carbohydrates
- Vaginal candidiasis
- Change in corneal curvature (steepening)
- Intolerance to contact lenses

The following adverse reactions have been reported in users of oral contraceptives and the association has been neither confirmed nor refuted:

- Pre-menstrual syndrome
- Cataracts
- Changes in appetite
- Cystitis-like syndrome
- Headache
- Nervousness
- Dizziness
- Hirsutism
- Loss of scalp hair
- Erythema multiforme
- Erythema nodosum
- Hemorrhagic eruption
- Vaginitis
- Porphyria
- Impaired renal function
- Hemolytic uremic syndrome
- Budd-Chiari syndrome
- Acne
- Changes in libido
- Colitis

OVERDOSAGE

Serious ill effects have not been reported following acute ingestion of large doses of oral contraceptives by young children. Overdosage may cause nausea, and withdrawal bleeding may occur in females.

NON-CONTRACEPTIVE HEALTH BENEFITS

The following non-contraceptive health benefits related to the use of oral contraceptives are supported by epidemiological studies which largely utilized oral contraceptive formulations containing estrogen doses exceeding 0.035 mg of ethinyl estradiol or 0.05 mg of mestranol.^6-11

Effects on Menses:

- Increased menstrual cycle regularity
- Decreased blood loss and decreased incidence of iron deficiency anemia
- Decreased incidence of dysmenorrhea

Effects Related to Inhibition of Ovulation:

- Decreased incidence of functional ovarian cysts
- Decreased incidence of ectopic pregnancies

Effects From Long-Term Use:

- Decreased incidence of fibroadenomas and fibrocystic disease of the breast
- Decreased incidence of acute pelvic inflammatory disease
- Decreased incidence of endometrial cancer
- Decreased incidence of ovarian cancer

DOSAGE AND ADMINISTRATION

To achieve maximum contraceptive effectiveness, oral contraceptives must be taken exactly as directed and at intervals not exceeding 24 hours.

For a DAY 1 START, count the first day of menstrual flow as Day 1 and the first light yellow tablet is then taken on Day 1. For a SUNDAY START when menstrual flow begins on or before Sunday, the first light yellow tablet is taken on that day. With either a DAY 1 START or SUNDAY START, 1 light yellow tablet is taken for 7 days, then 1 white tablet for 9 days, then 1 light yellow tablet for 5 days, then 1 peach tablet (inert) for 7 days, whether bleeding has stopped or not. With either a DAY 1 START or SUNDAY START 1 tablet is taken each day at the same time for 28 days. After all 28 tablets are taken, whether bleeding has stopped or not, the same dosage schedule is repeated beginning on the following day.

INSTRUCTIONS TO PATIENTS

- To achieve maximum contraceptive effectiveness, the oral contraceptive pill must be taken exactly as directed and at intervals not exceeding 24 hours.
- Important: Women should be instructed to use an additional method of protection until after the first 7 days of administration in the initial cycle.
- Due to the normally increased risk of thromboembolism occurring postpartum, women should be instructed not to initiate treatment with oral contraceptives earlier than 4 weeks after a full-term delivery. If pregnancy is terminated in the first 12 weeks, the patient should be instructed to start oral contraceptives immediately or within 7 days. If pregnancy is terminated after 12 weeks, the patient should be instructed to start oral contraceptives after 2 weeks.^(33, 77)
- If spotting or breakthrough bleeding should occur, the patient should continue the medication according to the schedule. Should spotting or breakthrough bleeding persist, the patient should notify her physician.
- If the patient misses 1 pill, she should be instructed to take it as soon as she remembers and then take the next pill at the regular time. The patient should be advised that missing a pill can cause spotting or light bleeding and that she may be a little sick to her stomach on the days she takes the missed pill with her regularly scheduled pill. If the patient has missed more than one pill, see DETAILED PATIENT LABELING, HOW TO TAKE THE PILL, WHAT TO DO IF YOU MISS PILLS.
- Use of oral contraceptives in the event of a missed menstrual period:
- If the patient has not adhered to the prescribed dosage regimen, the possibility of
  pregnancy should be considered after the first missed period and oral contraceptives should
  be withheld until pregnancy has been ruled out.
- If the patient has adhered to the prescribed regimen and misses 2 consecutive periods,
  pregnancy should be ruled out before continuing the contraceptive regimen.

HOW SUPPLIED

Aranelle® - 28-Day Regimen (norethindrone and ethinyl estradiol tablets USP 0.5/0.035 mg and 1/0.035 mg) – Each blister card contains 12 light yellow, round, flat-faced, beveled-edge, unscored tablets, debossed with stylized b on one side and 341 on the other side each containing 0.5 mg norethindrone and 0.035 mg ethinyl estradiol; 9 white, round, flat-faced, beveled-edge, unscored tablets, debossed with stylized b on one side and 342 on the other side each containing 1 mg norethindrone and 0.035 mg ethinyl estradiol; and 7 peach, round, flat-faced, beveled-edge, unscored placebo tablets, debossed with stylized b on one side and 343 on the other side. The first row contains 7 light yellow tablets; the second row contains 7 white tablets; the third row contains 2 white and 5 light yellow tablets and the fourth row contains 7 peach inert tablets.

Available in a box of 3 blister cards (NDC: 0555-9066-67).

Store at 20° to 25°C (68° to 77°F) [See USP Controlled Room Temperature].

Keep this and all medications out of the reach of children.

REFERENCES

1. Hatcher, R.A. Trussell, J. Stewart, F., et al.: Contraceptive Technology: Seventeenth Revised Edition, New York, NY, 1998. 2. Mann, J., et al.: Br Med J 2(5956): 241-245, 1975. 3. Knopp, R.H.: J Reprod Med 31(9): 913-921, 1986. 4. Mann, J.I., et al.: Br Med J 2: 445-447, 1976. 5. Ory, H.: JAMA 237: 2619-2622, 1977. 6. The Cancer and Steroid Hormone Study of the Centers for Disease Control: JAMA 249(2): 1596-1599, 1983. 7. The Cancer and Steroid Hormone Study of the Centers for Disease Control: JAMA 257(6): 796-800, 1987. 8. Ory, H.W.: JAMA 228(1): 68-69, 1974. 9. Ory, H.W., et al.: N Engl J Med 294: 419-422, 1976. 10. Ory, H.W.: Fam Plann Perspect 14: 182-184, 1982. 11. Ory, H.W., et al.: Making Choices, New York, The Alan Guttmacher Institute, 1983. 12. Stadel, B.: N Engl J Med 305(11): 612-618, 1981. 13. Stadel, B.: N Engl J Med 305(12): 672-677, 1981. 14. Adam, S., et al.: Br J Obstet Gynaecol 88: 838-845,1981. 15. Mann, J., et al.: Br Med J 2(5965): 245-248, 1975. 16. Royal College of General Practitioners’ Oral Contraceptive Study: Lancet 1: 541-546, 1981. 17. Slone, D., et al.: N Engl J Med 305(8): 420-424, 1981. 18. Vessey, M.P.: Br J Fam Plann 6 (supplement): 1-12, 1980. 19. Russell-Briefel, R., et al.: Prev Med 15: 352-362, 1986. 20. Goldbaum, G., et al.: JAMA 258(10): 1339-1342, 1987. 21. LaRosa, J.C.: J Reprod Med 31 (9): 906-912, 1986. 22. Krauss, R.M., et al.: Am J Obstet Gynecol 145: 446-452, 1983. 23. Wahl, P., et al.: N Engl J Med 308(15): 862-867, 1983. 24. Wynn, V., et al.: Am J Obstet Gynecol 142(6): 766-771, 1982. 25. Wynn, V., et al.: J Reprod Med 31(9): 892-897, 1986. 26. Inman, W.H., et al.: Br Med J 2(5599): 193-199, 1968. 27. Maguire, M.G., et al.: Am J Epidemiol 110(2): 188-195, 1979. 28. Petitti, D., et al.: JAMA 242(11): 1150-1154, 1979. 29. Vessey, M.P., et al.: Br Med J 2(5599): 199-205, 1968. 30. Vessey, M.P., et al.: Br Med J 2(5658): 651-657, 1969. 31. Porter, J.B., et al.: Obstet Gynecol 59(3): 299-302, 1982. 32. Vessey, M.P., et al.: J Biosoc Sci 8: 373-427, 1976. 33. Mishell, D.R., et al.: Reproductive Endocrinology, Philadelphia, F.A. Davis Co., 1979. 34. Petitti, D.B., et al.: Lancet 2: 234-236, 1978. 35. Collaborative Group for the Study of Stroke in Young Women: JAMA 231(7): 718-722, 1975. 36. Inman, W.H., et al.: Br Med J 2: 203-209, 1970. 37. Meade, T.W., et al.: Br Med J 280(6224): 1157-1161, 1980. 38. Kay, C.R.: Am J Obstet Gynecol 142(6): 762-765, 1982. 39. Gordon, T., et al.: Am J Med 62: 707-714, 1977. 40. Royal College of General Practitioners’ Oral Contraception Study: J Coll Gen Pract 33: 75-82, 1983. 41. Ory, H.W.: Fam Plann Perspect 15(2): 57-63, 1983. 42. Paul, C., et al.: Br Med J 293: 723-725, 1986. 43. The Cancer and Steroid Hormone Study of the Centers for Disease Control: N Engl J Med 315(7): 405-411, 1986. 44. Pike, M.C., et al.: Lancet 2: 926-929, 1983. 45. Miller, D.R., et al.: Obstet Gynecol 68: 863-868, 1986. 46. Olsson, H., et al.: Lancet 2: 748-749, 1985. 47. McPherson, K., et al.: Br J Cancer 56: 653-660, 1987. 48. Huggins, G.R., et al.: Fertil Steril 47(5): 733-761, 1987. 49. McPherson, K., et al.: Br Med J 293: 709-710, 1986. 50. Ory, H., et al.: Am J Obstet Gynecol 124(6): 573-577, 1976. 51. Vessey, M.P., et al.: Lancet 2: 930, 1983. 52. Brinton, L.A., et al.: Int J Cancer 38: 339-344, 1986. 53. WHO Collaborative Study of Neoplasia and Steroid Contraceptives: Br Med J 290: 961-965, 1985. 54. Rooks, J.B., et al.: JAMA 242(7): 644-648, 1979. 55. Bein, N.N., et al.: Br J Surg 64: 433-435, 1977. 56. Klatskin, G.: Gastroenterology 73: 386-394, 1977. 57. Henderson, B.E., et al.: Br J Cancer 48: 437-440, 1983. 58. Neuberger, J., et al.: Br Med J 292: 1355-1357, 1986. 59. Forman, D., et al.: Br Med J 292: 1357-1361, 1986. 60. Harlap, S., et al.: Obstet Gynecol 55(4): 447-452, 1980. 61. Savolainen, E., et al.: Am J Obstet Gynecol 140(5): 521-524, 1981. 62. Janerich, D.T., et al.: Am J Epidemiol 112(1): 73-79, 1980. 63. Ferencz, C., et al.: Teratology 21: 225-239, 1980. 64. Rothman, K.J., et al.: Am J Epidemiol 109(4): 433-439, 1979. 65. Boston Collaborative Drug Surveillance Program: Lancet 1: 1399-1404, 1973. 66. Royal College of General Practitioners: Oral contraceptives and health. New York, Pittman, 1974. 67. Rome Group for the Epidemiology and Prevention of Cholelithiasis: Am J Epidemiol 119(5): 796-805, 1984. 68. Strom, B.L., et al.: Clin Pharmacol Ther 39(3): 335-341, 1986. 69. Perlman, J.A., et al.: J Chronic Dis 38(10): 857-864, 1985. 70. Wynn, V., et al.: Lancet 1: 1045-1049, 1979. 71. Wynn, V.: Progesterone and Progestin, New York, Raven Press, 1983. 72. Wynn, V., et al.: Lancet 2: 720-723, 1966. 73. Fisch, I.R., et al.: JAMA 237(23): 2499-2503, 1977. 74. Laragh, J.H.: Am J Obstet Gynecol 126(1): 141-147, 1976. 75. Ramcharan, S., et al.: Pharmacology of Steroid Contraceptive Drugs, New York, Raven Press, 1977. 76. Stockley, I.: Pharm J 216: 140-143, 1976. 77. Dickey, R.P.: Managing Contraceptive Pill Patients, Oklahoma, Creative Informatics Inc., 1984. 78. Porter J.B., Hunter J., Jick H., et al.: Obstet Gynecol 1985; 66: 1-4. 79. Porter J.B., Hershel J., Walker A.M.: Obstet Gynecol 1987; 70: 29-32. 80. Fertility and Maternal Health Drugs Advisory Committee, F.D.A., October, 1989. 81. Schlesselman J., Stadel B.V., Murray P., Lai S.: Breast cancer in relation to early use of oral contraceptives. JAMA 1988; 259: 1828-1833. 82. Hennekens C.H., Speizer F.E., Lipnick R.J., Rosner B., Bain C., Belanger C., Stampfer M.J., Willett W., Peto R.: A case-control study of oral contraceptive use and breast cancer. JNCI 1984; 72: 39-42. 83. Royal College of General Practitioners: Oral contraceptives, venous thrombosis, and varicose veins. J Coll Gen Pract 28: 393-399, 1978. 84. Royal College of General Practitioners’ Oral Contraception Study: Effect on Hypertension and benign breast disease of progestogen component in combined oral contraceptives. Lancet 1: 624, 1977.

Teva Pharmaceuticals USA, Inc.

North Wales, PA 19454

Rev. D 1/2023

DETAILED PATIENT LABELING

This product (like all oral contraceptives) is intended to prevent pregnancy. It does not protect against HIV infection (AIDS) and other sexually transmitted diseases.

INTRODUCTION

Any woman who considers using oral contraceptives (“birth control pills” or “the pill”) should understand the benefits and risks of using this form of birth control. This leaflet will give you much of the information you will need to make this decision and also will help you determine if you are at risk of developing any of the serious side effects of the pill. It will tell you how to use the pill properly so that it will be as effective as possible. However, this leaflet is not a replacement for a careful discussion between you and your health care provider. You should discuss the information provided in this leaflet with him or her, both when you first start taking the pill and during your regular visits. You also should follow the advice of your health care provider with regard to regular checkups while you are on the pill.

EFFECTIVENESS OF ORAL CONTRACEPTIVES

Oral contraceptives are used to prevent pregnancy and are more effective than other non-surgical methods of birth control. When they are taken correctly, without missing any pills, the chance of becoming pregnant is less than 1% (1 pregnancy per 100 women per year of use). Typical failure rates are actually 3% per year. The chance of becoming pregnant increases with each missed pill during a menstrual cycle.

In comparison, typical failure rates for other nonsurgical methods of birth control during the first year are as follows:

TABLE I: PERCENTAGE OF WOMEN EXPERIENCING AN UNINTENDED PREGNANCY DURING THE FIRST YEAR OF TYPICAL USE AND THE FIRST YEAR OF PERFECT USE OF CONTRACEPTION AND THE PERCENTAGE CONTINUING USE AT THE END OF THE FIRST YEAR. UNITED STATES.
 | % of Women Experiencing an Unintended Pregnancy within the First Year of Use |  | % of Women Continuing Use at One Year^3
Method; (1) | Typical Use^1; (2) | Perfect Use^2; (3) | (4)
Chance^4 | 85 | 85
Spermicides^5 | 26 | 6 | 40
Periodic abstinence | 25 |  | 63
Calendar |  | 9
Ovulation method |  | 3
Sympto-thermal^6 |  | 2
Post-ovulation |  | 1
Withdrawal | 19 | 4
Cap^7
Parous women | 40 | 26 | 42
Nulliparous women | 20 | 9 | 56
Sponge
Parous women | 40 | 20 | 42
Nulliparous women | 20 | 9 | 56
Diaphragm^7 | 20 | 6 | 56
Condom^8
Female (Reality) | 21 | 5 | 56
Male | 14 | 3 | 61
Pill | 5 |  | 71
Progestin only |  | 0.5
Combined |  | 0.1
IUD
Progesterone T | 2 | 1.5 | 81
Copper T 380A | 0.8 | 0.6 | 78
LNg 20 | 0.1 | 0.1 | 81
Depo-Provera | 0.3 | 0.3 | 70
Norplant and Norplant-2 | 0.05 | 0.05 | 88
Female sterilization | 0.5 | 0.5 | 100
Male sterilization | 0.15 | 0.10 | 100
Emergency Contraceptive Pills: Treatment initiated within 72 hours after unprotected intercourse reduces the risk of pregnancy by at least 75%.^9
Lactational Amenorrhea Method: LAM is a highly effective, temporary method of contraception^10
Source: Trussell J. Contraceptive Efficacy Table from Hatcher R.A., Trussell J, Stewart F, Cates W, Stewart GK, Kowal D, Guest F, in Contraceptive Technology: Seventeenth Revised Edition. New York, NY: Irvington Publishers, 1998.
1. Among typical couples who initiate use of a method (not necessarily for the first time), the percentage who experience an accidental pregnancy during the first year if they do not stop use for any other reason.
2. Among couples who initiate use of a method (not necessarily for the first time) and who use it perfectly (both consistently and correctly), the percentage who experience an accidental pregnancy during the first year if they do not stop use for any other reason.
3. Among couples attempting to avoid pregnancy, the percentage who continue to use a method for one year.
4. The percents becoming pregnant in columns (2) and (3) are based on data from populations where contraception is not used and from women who cease using contraception in order to become pregnant. Among such populations, about 89% become pregnant within one year. This estimate was lowered slightly (to 85%) to represent the percent who would become pregnant within one year among women now relying on reversible methods of contraception if they abandoned contraception altogether.
5. Foams, creams, gels, vaginal suppositories, and vaginal film.
6. Cervical mucus (ovulation) method supplemented by calendar in the pre-ovulatory and basal body temperature in the post-ovulatory phases.
7. With spermicidal cream or jelly.
8. Without spermicides.
9. The treatment schedule is one dose within 72 hours after unprotected intercourse and a second dose 12 hours after the first dose. The Food and Drug Administration has declared the following brands of oral contraceptives to be safe and effective for emergency contraception: Ovral (1 dose is 2 white pills), Alesse (1 dose is 5 pink pills), Nordette or Levlen (1 dose is 2 light-orange pills), Lo/Ovral (1 dose is 4 white pills), Triphasil or Tri-Levlen (1 dose is 4 yellow pills).
10. However, to maintain effective protection against pregnancy, another method of contraception must be used as soon as menstruation resumes, the frequency or duration of breastfeeds is reduced, bottle feeds are introduced, or the baby reaches six months of age.

WHO SHOULD NOT TAKE ORAL CONTRACEPTIVES

Cigarette smoking increases the risk of serious cardiovascular side effects from oral contraceptive use. This risk increases with age and with heavy smoking (15 or more cigarettes per day) and is quite marked in women over 35 years of age. Women who use oral contraceptives are strongly advised not to smoke.

Some women should not use the pill. For example, you should not take the pill if you are pregnant or think you may be pregnant. You also should not use the pill if you have any of the following conditions:

- A history of heart attack or stroke
- Blood clots in the legs (thrombophlebitis), brain (stroke), lungs (pulmonary embolism) or eyes
- A history of blood clots in the deep veins of your legs
- Chest pain (angina pectoris)
- Known or suspected breast cancer or cancer of the lining of the uterus, cervix or vagina
- Unexplained vaginal bleeding (until a diagnosis is reached by your doctor)
- Yellowing of the whites of the eyes or of the skin (jaundice) during pregnancy or during previous use of the pill
- Liver tumor (benign or cancerous)
- Known or suspected pregnancy
- Take any Hepatitis C drug combination containing ombitasvir/paritaprevir/ritonavir, with or without dasabuvir. This may increase levels of the liver enzyme “alanine aminotransferase” (ALT) in the blood.

Tell your health care provider if you have ever had any of these conditions. Your health care provider can recommend a safer method of birth control.

OTHER CONSIDERATIONS BEFORE TAKING ORAL CONTRACEPTIVES

Tell your health care provider if you have or have had:

- Breast nodules, fibrocystic disease of the breast, an abnormal breast x-ray or mammogram
- Diabetes
- Elevated cholesterol or triglycerides
- High blood pressure
- Migraine or other headaches or epilepsy
- Mental depression
- Gallbladder, heart or kidney disease
- History of scanty or irregular menstrual periods

Women with any of these conditions should be checked often by their health care provider if they choose to use oral contraceptives.

Also, be sure to inform your doctor or health care provider if you smoke or are on any medications.

RISKS OF TAKING ORAL CONTRACEPTIVES

1. Risk of developing blood clots

Blood clots and blockage of blood vessels are the most serious side effects of taking oral contraceptives. In particular, a clot in the legs can cause thrombophlebitis and a clot that travels to the lungs can cause a sudden blocking of the vessel carrying blood to the lungs. Rarely, clots occur in the blood vessels of the eye and may cause blindness, double vision, or impaired vision.

If you take oral contraceptives and need elective surgery, need to stay in bed for a prolonged illness or have recently delivered a baby, you may be at risk of developing blood clots. You should consult your doctor about stopping oral contraceptives three to four weeks before surgery and not taking oral contraceptives for two weeks after surgery or during bed rest. You should also not take oral contraceptives soon after delivery of a baby. It is advisable to wait for at least four weeks after delivery if you are not breast feeding. If you are breast feeding, you should wait until you have weaned your child before using the pill (see GENERAL PRECAUTIONS, While breast feeding).

2. Heart attacks and strokes

Oral contraceptives may increase the tendency to develop strokes (stoppage or rupture of blood vessels in the brain) and angina pectoris and heart attacks (blockage of blood vessels in the heart). Any of these conditions can cause death or temporary or permanent disability.

Smoking greatly increases the possibility of suffering heart attacks and strokes. Furthermore, smoking and the use of oral contraceptives greatly increase the chances of developing and dying of heart disease.

3. Gallbladder disease

Oral contraceptive users may have a greater risk than non-users of having gallbladder disease, although this risk may be related to pills containing high doses of estrogen.

4. Liver tumors

In rare cases, oral contraceptives can cause benign but dangerous liver tumors. These benign liver tumors can rupture and cause fatal internal bleeding. In addition, a possible but not definite association has been found with the pill and liver cancers in 2 studies in which a few women who developed these very rare cancers were found to have used oral contraceptives for long periods. However, liver cancers are extremely rare. The chance of developing liver cancer from using the pill is thus even rarer.

5. Risk of Cancer

It is not known if hormonal birth control pills cause breast cancer. Some studies, but not all, suggest that there could be a slight increase in the risk of breast cancer among current users with longer duration of use.

If you have breast cancer now, or have had it in the past, do not use hormonal birth control because some breast cancers are sensitive to hormones.

Some studies have found an increase in the incidence of cancer of the cervix in women who use oral contraceptives. However, this finding may be related to factors other than the use of oral contraceptives.

ESTIMATED RISK OF DEATH FROM A BIRTH CONTROL METHOD OR PREGNANCY

All methods of birth control and pregnancy are associated with a risk of developing certain diseases which may lead to disability or death. An estimate of the number of deaths associated with different methods of birth control and pregnancy has been calculated and is shown in the following table:

Table II: ESTIMATED ANNUAL NUMBER OF BIRTH-RELATED OR METHOD-RELATED DEATHS ASSOCIATED WITH CONTROL OF FERTILITY PER 100,000 NON-STERILE WOMEN, BY FERTILITY CONTROL METHOD ACCORDING TO AGE.
 |  |  | Age
Method of Control and Outcome | 15 to 19 | 20 to 24 | 25 to 29 | 30 to 34 | 35 to 39 | 40 to 44
No fertility control methods* | 7 | 7.4 | 9.1 | 14.8 | 25.7 | 28.2
Oral contraceptives nonsmoker** smoker** | 0.3 2.2 | 0.5 3.4 | 0.9 6.6 | 1.9 13.5 | 13.8 51.1 | 31.6 117.2
IUD** | 0.8 | 0.8 | 1 | 1 | 1.4 | 1.4
Condom* | 1.1 | 1.6 | 0.7 | 0.2 | 0.3 | 0.4
Diaphragm/Spermicide* | 1.9 | 1.2 | 1.2 | 1.3 | 2.2 | 2.8
Periodic abstinence* | 2.5 | 1.6 | 1.6 | 1.7 | 2.9 | 3.6

* Deaths are birth-related
** Deaths are method-related
Estimates adapted from H.W. Ory, Table 3 ^41

In the above table, the risk of death from any birth control method is less than the risk of childbirth except for oral contraceptive users over the age of 35 who smoke and pill users over the age of 40 even if they do not smoke. It can be seen from the table that for women aged 15 to 39 the risk of death is highest with pregnancy (7 to 26 deaths per 100,000 women, depending on age). Among pill users who do not smoke the risk of death is always lower than that associated with pregnancy for any age group, although over the age of 40 the risk increases to 32 deaths per 100,000 women compared to 28 associated with pregnancy at that age. However, for pill users who smoke and are over the age of 35 the estimated number of deaths exceeds those for other methods of birth control. If a woman is over the age of 40 and smokes, her estimated risk of death is 4 times higher (117/100,000 women) than the estimated risk associated with pregnancy (28/100,000 women) in that age group.

The suggestion that women over 40 who don’t smoke should not take oral contraceptives is based on information from older high-dose pills and on less selective use of pills than is practiced today. An Advisory Committee of the FDA discussed this issue in 1989 and recommended that the benefits of oral contraceptive use by healthy, non-smoking women over 40 years of age may outweigh the possible risks. However, all women, especially older women, are cautioned to use the lowest dose pill that is effective.

WARNING SIGNALS

If any of these adverse effects occur while you are taking oral contraceptives, call your doctor immediately:

- Sharp chest pain, coughing of blood or sudden shortness of breath (indicating a possible clot in the lung)
- Pain in the calf (indicating a possible clot in the leg)
- Crushing chest pain or heaviness in the chest (indicating a possible heart attack)
- Sudden severe headache or vomiting, dizziness or fainting, disturbances of vision or speech, weakness or numbness in an arm or leg (indicating a possible stroke)
- Sudden partial or complete loss of vision (indicating a possible clot in the eye)
- Breast lumps (indicating possible breast cancer or fibrocystic disease of the breast: ask your doctor or health care provider to show you how to examine your breasts)
- Severe pain or tenderness in the stomach area (indicating a possible ruptured liver tumor)
- Difficulty in sleeping, weakness, lack of energy, fatigue or change in mood (possibly indicating severe depression)
- Jaundice or a yellowing of the skin or eyeballs, accompanied frequently by fever, fatigue, loss of appetite, dark colored urine or light colored bowel movements (indicating possible liver problems)

SIDE EFFECTS OF ORAL CONTRACEPTIVES

1. Vaginal bleeding

Irregular vaginal bleeding or spotting may occur while you are taking the pill. Irregular bleeding may vary from slight staining between menstrual periods to breakthrough bleeding which is a flow much like a regular period. Irregular bleeding occurs most often during the first few months of oral contraceptive use but may also occur after you have been taking the pill for some time. Such bleeding may be temporary and usually does not indicate any serious problem. It is important to continue taking your pills on schedule. If the bleeding occurs in more than 1 cycle or lasts for more than a few days, talk to your doctor or health care provider.

2. Contact lenses

If you wear contact lenses and notice a change in vision or an inability to wear your lenses, contact your doctor or health care provider.

3. Fluid retention

Oral contraceptives may cause edema (fluid retention) with swelling of the fingers or ankles and may raise your blood pressure. If you experience fluid retention, contact your doctor or health care provider.

4. Melasma (Mask of Pregnancy)

A spotty darkening of the skin is possible, particularly of the face.

5. Other side effects

Other side effects may include change in appetite, headache, nervousness, depression, dizziness, loss of scalp hair, rash and vaginal infections.

If any of these side effects occurs, contact your doctor or health care provider.

GENERAL PRECAUTIONS

1. Missed periods and use of oral contraceptives before or during early pregnancy

At times you may not menstruate regularly after you have completed taking a cycle of pills. If you have taken your pills regularly and miss 1 menstrual period, continue taking your pills for the next cycle but be sure to inform your health care provider before doing so. If you have not taken the pills daily as instructed and miss 1 menstrual period, or if you miss 2 consecutive menstrual periods, you may be pregnant. Check with your health care provider immediately to determine whether you are pregnant. Do not continue to take oral contraceptives until you are sure you are not pregnant, but continue to use another method of birth control.

There is no conclusive evidence that oral contraceptive use is associated with an increase in birth defects when taken inadvertently during early pregnancy. Previously, a few studies had reported that oral contraceptives might be associated with birth defects but these studies have not been confirmed. Nevertheless, oral contraceptives or any other drugs should not be used during pregnancy unless clearly necessary and prescribed by your doctor. You should check with your doctor about risks to your unborn child from any medication taken during pregnancy.

2. While breast feeding

If you are breast feeding, consult your doctor before starting oral contraceptives. Some of the drug will be passed on to the child in the milk. A few adverse effects on the child have been reported, including yellowing of the skin (jaundice) and breast enlargement. In addition, oral contraceptives may decrease the amount and quality of your milk. If possible, do not use oral contraceptives and use another method of contraception while breast feeding. You should consider starting oral contraceptives only after you have weaned your child completely.

3. Laboratory tests

If you are scheduled for any laboratory tests, tell your doctor you are taking birth control pills. Certain blood tests may be affected by birth control pills.

4. Drug interactions

Certain drugs may interact with birth control pills to make them less effective in preventing pregnancy or cause an increase in breakthrough bleeding. Such drugs include rifampin; drugs used for epilepsy such as barbiturates (for example phenobarbital) and phenytoin (Dilantin is one brand of this drug); phenylbutazone (Butazolidin is one brand of this drug) and possibly certain antibiotics. You may need to use additional contraception when you take drugs which can make oral contraceptives less effective.

5. This product (like all oral contraceptives) is intended to prevent pregnancy. It does not protect against transmission of HIV (AIDS) and other sexually transmitted diseases such as chlamydia, genital herpes, genital warts, gonorrhea, hepatitis B, and syphilis.

HOW TO TAKE THE PILL

IMPORTANT POINTS TO REMEMBER

BEFORE YOU START TAKING YOUR PILLS:

1. BE SURE TO READ THESE DIRECTIONS:
  - Before you start taking your pills.
  - Anytime you are not sure what to do.
2. THE RIGHT WAY TO TAKE THE PILL IS TO TAKE ONE PILL EVERY DAY AT THE SAME TIME.
  If you miss pills you could get pregnant. This includes starting the pack late.
  The more pills you miss, the more likely you are to get pregnant.
3. MANY WOMEN HAVE SPOTTING OR LIGHT BLEEDING, OR MAY FEEL SICK TO THEIR STOMACH DURING THE FIRST 1 to 3 PACKS OF PILLS.
  If you feel sick to your stomach, do not stop taking the pill. The problem will usually go away. If it doesn't go away, check with your doctor or clinic.
4. MISSING PILLS CAN ALSO CAUSE SPOTTING OR LIGHT BLEEDING, even when you make up these missed pills.
  On the days you take 2 pills to make up for missed pills, you could also feel a little sick to your stomach.
5. IF YOU HAVE VOMITING OR DIARRHEA, for any reason, or IF YOU TAKE SOME MEDICINES, including some antibiotics, your pills may not work as well.
  Use a back-up method (such as condoms, foam, or sponge) until you check with your doctor or clinic.
6. IF YOU HAVE TROUBLE REMEMBERING TO TAKE THE PILL, talk to your doctor or clinic about how to make pill-taking easier or about using another method of birth control.
7. IF YOU HAVE ANY QUESTIONS OR ARE UNSURE ABOUT THE INFORMATION IN THIS LEAFLET, call your doctor or clinic.

BEFORE YOU START TAKING YOUR PILLS

1. DECIDE WHAT TIME OF DAY YOU WANT TO TAKE YOUR PILL.
  It is important to take it at about the same time every day.
2. LOOK AT YOUR PILL PACK TO SEE THAT IT HAS 28 PILLS
  The 28-pill pack has 21 “active” light yellow and white pills (with hormones) to take for 3 weeks, followed by 1 week of reminder peach pills (without hormones). To remove a pill, press down on it with your thumb or finger. The tablet will drop through the back of the tablet dispenser. Do not press on the tablet with your thumbnail, fingernail, or any other sharp object.
3. ALSO FIND:
  1) where on the pack to start taking the pills,
  2) in what order to take the pills (follow the arrows) and
  3) the week numbers as shown in the picture below.
  CHECK PICTURE OF THE FOLD-OVER DOSE CARD AND ADDITIONAL INSTRUCTIONS FOR USING THIS PACKAGE AT THE END OF THE BRIEF SUMMARY PATIENT PACKAGE INSERT.

Active pill colors: light yellow and white

Reminder pill color: peach

For use of Days of the Week Sticker, see WHEN TO START THE FIRST PACK OF PILLS below.

4. BE SURE YOU HAVE READY AT ALL TIMES:

- ANOTHER KIND OF BIRTH CONTROL (such as condoms, foam, or sponge) to use as
  a back-up in case you miss pills.
- AN EXTRA, FULL PILL PACK.

WHEN TO START THE FIRST PACK OF PILLS

You have a choice of which day to start taking your first pack of pills. Decide with your doctor or clinic which is the best day for you. Pick a time of day which will be easy to remember.

DAY 1 START:

1. Pick the Days of the Week Sticker that starts with the first day of your period. Place this Days of the Week Sticker over the area that has the days of the week (starting with Sunday) pre-printed on the tablet dispenser. Note: if the first day of your period is a Sunday, you can skip step #1.
2. Take the first “active” light yellow pill of the first pack during the first 24 hours of your period.
3. You will not need to use a back-up method of birth control, since you are starting the pill at the beginning of your period.

SUNDAY START:

1. Take the first “active” light yellow pill of the first pack on the Sunday after your period starts, even if you are still bleeding. If your period begins on Sunday, start the pack that same day.
2. Use another method of birth control as a back-up method if you have sex anytime from the Sunday you start your first pack until the next Sunday (7 days). Condoms, foam, or the sponge are good back-up methods of birth control.

WHAT TO DO DURING THE MONTH

1. TAKE ONE PILL AT THE SAME TIME EVERY DAY UNTIL THE PACK IS EMPTY.
  - Do not skip pills even if you are spotting or bleeding between monthly periods or feel sick to your stomach (nausea).
  - Do not skip pills even if you do not have sex very often.
2. WHEN YOU FINISH A PACK OR SWITCH YOUR BRAND OF PILLS:
  - Start the next pack on the day after your last “reminder” pill. Do not wait any days between packs.

WHAT TO DO IF YOU MISS PILLS

If you MISS 1 light yellow or white “active” pill:

1. Take it as soon as you remember. Take the next pill at your regular time. This means you may take 2 pills in 1 day.
2. You do not need to use a back-up birth control method if you have sex.

If you MISS 2 light yellow or white “active” pills in a row in WEEK 1 OR WEEK 2 of your pack:

1. Take 2 pills on the day you remember and 2 pills the next day.
2. Then take 1 pill a day until you finish the pack.
3. You MAY BECOME PREGNANT if you have sex in the 7 days after you miss pills. You MUST use another birth control method (such as condoms, foam, or sponge) as a back-up for those 7 days.

If you MISS 2 light yellow or white “active” pills in a row in THE 3rd WEEK:

1. If you are a Day 1 Starter:
  THROW OUT the rest of the pill pack and start a new pack that same day.
  If you are a Sunday Starter:
  Keep taking 1 pill every day until Sunday.
  On Sunday, THROW OUT the rest of the pack and start a new pack of pills that same day.
2. You may not have your period this month but this is expected. However, if you miss your period 2 months in a row, call your doctor or clinic because you might be pregnant.
3. You MAY BECOME PREGNANT if you have sex in the 7 days after you miss pills. You MUST use another birth control method (such as condoms, foam, or sponge) as a back-up for those 7 days.

If you MISS 3 OR MORE light yellow or white “active” pills in a row (during the first 3 weeks):

1. If you are a Day 1 Starter:
  THROW OUT the rest of the pill pack and start a new pack of pills that same day.
  If you are a Sunday Starter:
  Keep taking 1 pill every day until Sunday.
  On Sunday, THROW OUT the rest of the pack and start a new pack of pills that same day.
2. You may not have your period this month but this is expected. However, if you miss your period 2 months in a row, call your doctor or clinic because you might be pregnant.
3. You MAY BECOME PREGNANT if you have sex in the 7 days after you miss pills. You MUST use another birth control method (such as condoms, foam, or sponge) as a back-up for those 7 days.

A REMINDER:

If you forget any of the 7 peach “reminder” pills in Week 4:

- THROW AWAY the pills you missed.
- Keep taking 1 pill each day until the pack is empty.
- You do not need a back-up method.

FINALLY, IF YOU ARE STILL NOT SURE WHAT TO DO ABOUT THE PILLS YOU HAVE MISSED:

- Use a BACK-UP METHOD anytime you have sex.
- KEEP TAKING ONE “ACTIVE” PILL EACH DAY until you can reach your doctor or
  clinic.

6. Missed periods, spotting or light bleeding

At times, you may not have a period after you have completed a pack of pills. If you miss 1 period but you have taken the pills exactly as you were supposed to, continue as usual into the next cycle. If you have not taken the pills correctly, and have missed a period, you may be pregnant and you should stop taking the pill until your doctor or clinic determines whether or not you are pregnant. Until you can talk to your doctor or clinic, use an appropriate back-up birth control method. If you miss 2 consecutive periods, you should stop taking the pill until it is determined that you are not pregnant.
Even if spotting or light bleeding should occur, continue taking the pill according to the schedule. Should spotting or light bleeding persist, you should notify your doctor or clinic.

7. Stopping the pill before surgery or prolonged bed rest

If you are scheduled for surgery or you need to stay in bed for a long period of time you should tell your doctor that you are on the pill. You should stop taking the pill four weeks before your operation to avoid an increased risk of blood clots. Talk to your doctor about when you may start taking the pill again.

8. Starting the pill after pregnancy

After you have a baby it is advisable to wait 4 to 6 weeks before starting to take the pill. Talk to your doctor about when you may start taking the pill after pregnancy.

9. Pregnancy due to pill failure

When the pill is taken correctly, the expected pregnancy rate is approximately 1% (ie, 1 pregnancy per 100 women per year). If pregnancy occurs while taking the pill, there is little risk to the fetus. The typical failure rate of large numbers of pill users is less than 3% when women who have missed pills are included. If you become pregnant, you should discuss your pregnancy with your doctor.

10. Pregnancy after stopping the pill

There may be some delay in becoming pregnant after you stop taking the pill, especially if you had irregular periods before you started using the pill. Your doctor may recommend that you delay becoming pregnant until you have had one or more regular periods.
There does not appear to be any increase in birth defects in newborn babies when pregnancy occurs soon after stopping the pill.

11. Overdosage

There are no reports of serious illness or side effects in young children who have swallowed a large number of pills. In adults, overdosage may cause nausea and/or bleeding in females. In case of overdosage, contact your doctor, clinic or pharmacist.

12. Other information

Your doctor or clinic will take a medical and family history and will examine you before prescribing the pill. The physical examination may be delayed to another time if you request it and the health care provider believes that it is a good medical practice to postpone it. You should be reexamined at least once a year. Be sure to inform your doctor or clinic if there is a family history of any of the conditions listed previously in this leaflet. Be sure to keep all appointments with your doctor or clinic because this is a time to determine if there are early signs of side effects from using the pill.

Do not use the pill for any condition other than the one for which it was prescribed. The pill has been prescribed specifically for you, do not give it to others who may want birth control pills.
If you want more information about birth control pills, ask your doctor or clinic. They have a more technical leaflet called PHYSICIAN LABELING which you might want to read.

NON-CONTRACEPTIVE HEALTH BENEFITS

In addition to preventing pregnancy, use of oral contraceptives may provide certain non-contraceptive health benefits:

- Menstrual cycles may become more regular
- Blood flow during menstruation may be lighter and less iron may be lost. Therefore,
  anemia due to iron deficiency is less likely to occur
- Pain or other symptoms during menstruation may be encountered less frequently
- Ectopic (tubal) pregnancy may occur less frequently
- Non-cancerous cysts or lumps in the breast may occur less frequently
- Acute pelvic inflammatory disease may occur less frequently
- Oral contraceptive use may provide some protection against developing two forms of
  cancer: cancer of the ovaries and cancer of the lining of the uterus

Store at 20° to 25°C (68° to 77°F) [See USP Controlled Room Temperature].

Keep this and all medications out of the reach of children.

BRIEF SUMMARY – PATIENT PACKAGE INSERT

This product (like all oral contraceptives) is intended to prevent pregnancy. It does not protect against HIV infection (AIDS) and other sexually transmitted diseases.

Oral contraceptives, also known as “birth control pills” or “the pill”, are taken to prevent pregnancy and, when taken correctly, have a failure rate of about 1% per year when used without missing any pills. The typical failure rate of large numbers of pill users is less than 3% per year when women who miss pills are included. For most women, oral contraceptives are also free of serious or unpleasant side effects. However, forgetting to take oral contraceptives considerably increases the chances of pregnancy.

For the majority of women, oral contraceptives can be taken safely, but there are some women who are at high risk of developing certain serious diseases that can be life-threatening or may cause temporary or permanent disability. The risks associated with taking oral contraceptives increase significantly if you:

- Smoke
- Have high blood pressure, diabetes or high cholesterol
- Have or have had clotting disorders, heart attack, stroke, angina pectoris, cancer of the breast or sex organs, jaundice or malignant or benign liver tumors

You should not take the pill if you suspect you are pregnant or have unexplained vaginal bleeding.

Cigarette smoking increases the risk of serious cardiovascular side effects from oral contraceptive use. This risk increases with age and with heavy smoking (15 or more cigarettes per day) and is quite marked in women over 35 years of age. Women who use oral contraceptives are strongly advised not to smoke.

Most side effects of the pill are not serious. The most common such effects are nausea, vomiting, bleeding between menstrual periods, weight gain, breast tenderness, and difficulty wearing contact lenses. These side effects, especially nausea and vomiting, may subside within the first 3 months of use.

The serious side effects of the pill occur very infrequently, especially if you are in good health and are young. However, you should know that the following medical conditions have been associated with or made worse by the pill:

1. Blood clots in the legs (thrombophlebitis) or lungs (pulmonary embolism), stoppage or rupture of a blood vessel in the brain (stroke), blockage of blood vessels in the heart (heart attack or angina pectoris), eye or other organs of the body. As mentioned above, smoking increases the risk of heart attacks and strokes and subsequent serious medical consequences.
2. Liver tumors, which may rupture and cause severe bleeding. A possible but not definite association has been found with the pill and liver cancer. However, liver cancers are extremely rare. The chance of developing liver cancer from using the pill is thus even rarer.
3. High blood pressure, although blood pressure usually returns to normal when the pill is stopped.

The symptoms associated with these serious side effects are discussed in the detailed leaflet given to you with your supply of pills. Notify your doctor or health care provider if you notice any unusual physical disturbances while taking the pill. In addition, drugs such as rifampin, as well as some anti-convulsants and some antibiotics, may decrease oral contraceptive effectiveness.

There may be slight increases in the risk of breast cancer among current users of hormonal birth control pills with longer duration of use of 8 years or more.

Some studies have found an increase in the incidence of cancer of the cervix in women who use oral contraceptives. However, this finding may be related to factors other than the use of oral contraceptives.

Taking the pill provides some important non-contraceptive health benefits. These include less painful menstruation, less menstrual blood loss and anemia, fewer pelvic infections and fewer cancers of the ovary and the lining of the uterus.

Be sure to discuss any medical condition you may have with your health care provider. Your health care provider will take a medical and family history before prescribing oral contraceptives and will examine you. The physical examination may be delayed to another time if you request it and the health care provider believes that it is a good medical practice to postpone it. You should be reexamined at least once a year while taking oral contraceptives. The detailed patient information leaflet gives you further information which you should read and discuss with your health care provider.

HOW TO TAKE THE PILL

See full text of HOW TO TAKE THE PILL which is printed in full in the DETAILED PATIENT LABELING.

Call your doctor for medical advice about side effects. You may report side effects to Teva at
1-888-838-2872 or to FDA at 1-800-FDA-1088.

Teva Pharmaceuticals USA, Inc.
North Wales, PA 19454

Rev. D 1/2023

PRINCIPAL DISPLAY PANEL

NDC 0555-9066-67

3 Tablet Dispensers x 28 Tablets

28 DAY REGIMEN

Arnaelle® (norethindrone and ethinyl estradiol tablets USP) – triphasic regimen

Rx only

THIS PRODUCT (LIKE ALL ORAL CONTRACEPTIVES) IS INTENDED TO PREVENT PREGNANCY. IT DOES NOT PROTECT AGAINST HIV INFECTION (AIDS) AND OTHER SEXUALLY TRANSMITTED DISEASES.

PHARMACIST: Each foil pouch contains one combination “Detailed Patient Labeling/Brief Summary” insert which is provided to the patient with each prescription.

SHAPING WOMEN’S HEALTH®

TEVA